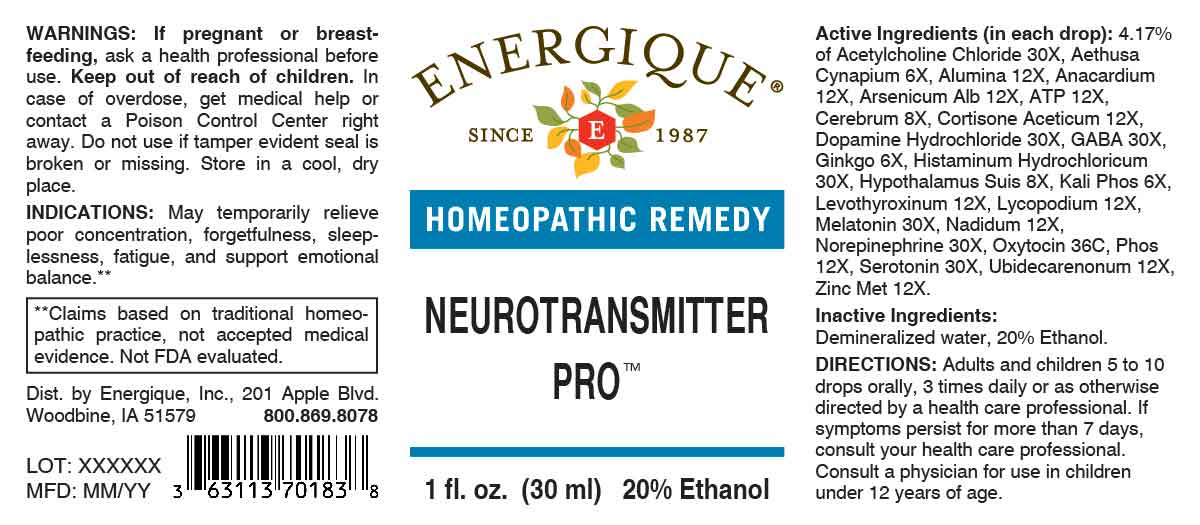 DRUG LABEL: Neurotransmitter Pro
NDC: 44911-0710 | Form: LIQUID
Manufacturer: Energique, Inc.
Category: homeopathic | Type: HUMAN OTC DRUG LABEL
Date: 20240506

ACTIVE INGREDIENTS: AETHUSA CYNAPIUM WHOLE 6 [hp_X]/1 mL; GINKGO 6 [hp_X]/1 mL; DIBASIC POTASSIUM PHOSPHATE 6 [hp_X]/1 mL; SUS SCROFA CEREBRUM 8 [hp_X]/1 mL; SUS SCROFA HYPOTHALAMUS 8 [hp_X]/1 mL; ADENOSINE TRIPHOSPHATE DISODIUM 12 [hp_X]/1 mL; ALUMINUM OXIDE 12 [hp_X]/1 mL; SEMECARPUS ANACARDIUM JUICE 12 [hp_X]/1 mL; ARSENIC TRIOXIDE 12 [hp_X]/1 mL; CORTISONE ACETATE 12 [hp_X]/1 mL; LEVOTHYROXINE 12 [hp_X]/1 mL; LYCOPODIUM CLAVATUM SPORE 12 [hp_X]/1 mL; NADIDE 12 [hp_X]/1 mL; PHOSPHORUS 12 [hp_X]/1 mL; UBIDECARENONE 12 [hp_X]/1 mL; ZINC 12 [hp_X]/1 mL; ACETYLCHOLINE CHLORIDE 30 [hp_X]/1 mL; DOPAMINE HYDROCHLORIDE 30 [hp_X]/1 mL; .GAMMA.-AMINOBUTYRIC ACID 30 [hp_X]/1 mL; HISTAMINE DIHYDROCHLORIDE 30 [hp_X]/1 mL; MELATONIN 30 [hp_X]/1 mL; NOREPINEPHRINE BITARTRATE 30 [hp_X]/1 mL; SEROTONIN HYDROCHLORIDE 30 [hp_X]/1 mL; OXYTOCIN 36 [hp_C]/1 mL
INACTIVE INGREDIENTS: WATER; ALCOHOL

DRUG FACTS:

ACTIVE INGREDIENT:

(in each drop): 4.17% of Acetylcholine Chloride 30X, Aethusa Cynapium 6X, Alumina 12X, Anacardium Orientale 12X, Arsenicum Album 12X, Adenosinum Triphosphoricum Dinatrum 12X, Cerebrum 8X, Cortisone Aceticum 12X, Dopamine Hydrochloride 30X, Gaba 30X, Ginkgo Biloba 6X, Histaminum Hydrochloricum 30X, Hypothalamus Suis 8X, Kali Phosphoricum 6X, Levothyroxinum 12X, Lycopodium Clavatum 12X, Melatonin 30X, Nadidum 12X, Norepinephrine 30X, Oxytocin 36C, Phosphorus 12X, Serotonin 30X, Ubidecarenonum 12X, Zincum Metallicum 12X.

PURPOSE:

May temporarily relieve poor concentration, forgetfulness, sleeplessness, fatigue, and support emotional balance.**

**Claims based on traditional homeopathic practice, not accepted medical evidence. Not FDA evaluated.

WARNINGS:

If pregnant or breast-feeding, ask a health professional before use.

Keep out of reach of children. In case of overdose, get medical help or contact a Poison Control Center right away.

Do not use if tamper evident seal is broken or missing. Store in a cool, dry place.

KEEP OUT OF REACH OF CHILDREN:

In case of overdose, get medical help or contact a Poison Control Center right away.

DIRECTIONS:

Adults and children 5 to 10 drops orally, 3 times daily or as otherwise directed by a health care professional. If symptoms persist for more than 7 days, consult your health care professional.

Consult a physician for use in children under 12 years of age.

INDICATIONS:

May temporarily relieve poor concentration, forgetfulness, sleeplessness, fatigue, and support emotional balance.**

**Claims based on traditional homeopathic practice, not accepted medical evidence. Not FDA evaluated.

INACTIVE INGREDIENTS:

Demineralized water, 20% Ethanol.

QUESTIONS:

Dist. by Energique, Inc.

201 Apple Blvd.

Woodbine, IA 51579

800.869.8078

PACKAGE LABEL DISPLAY:

ENERGIQUE

SINCE 1987

HOMEOPATHIC REMEDY

NEUROTRANSMITTER PRO™

1 fl. oz. (30 ml)